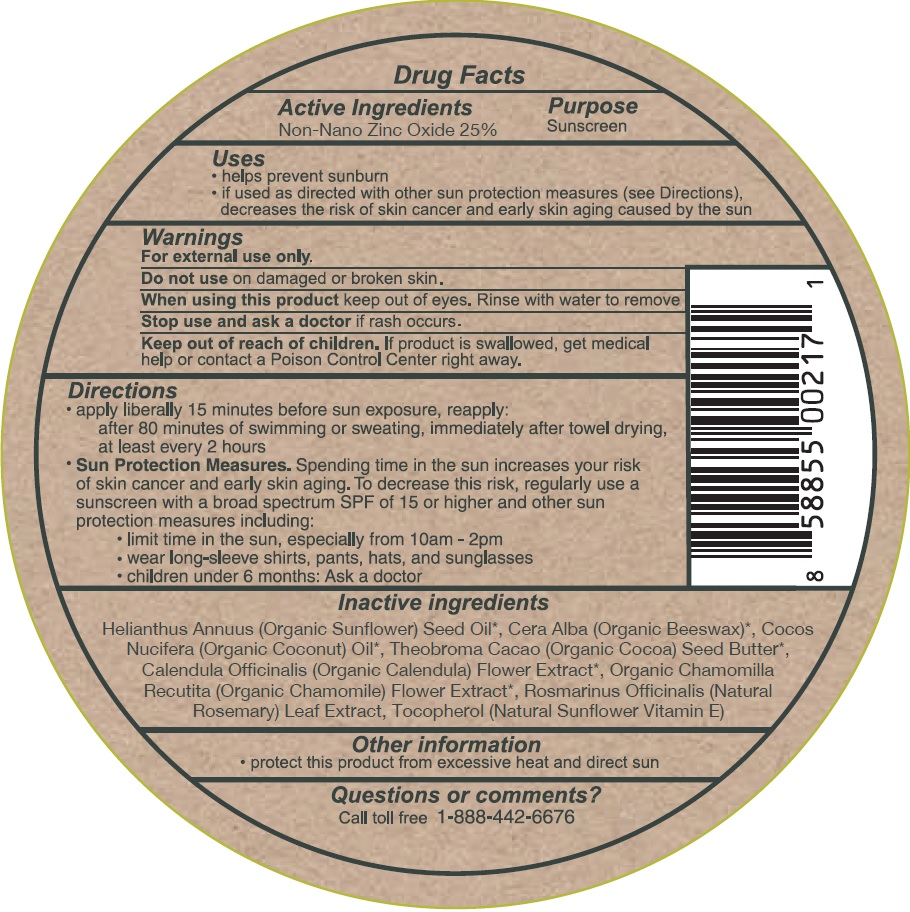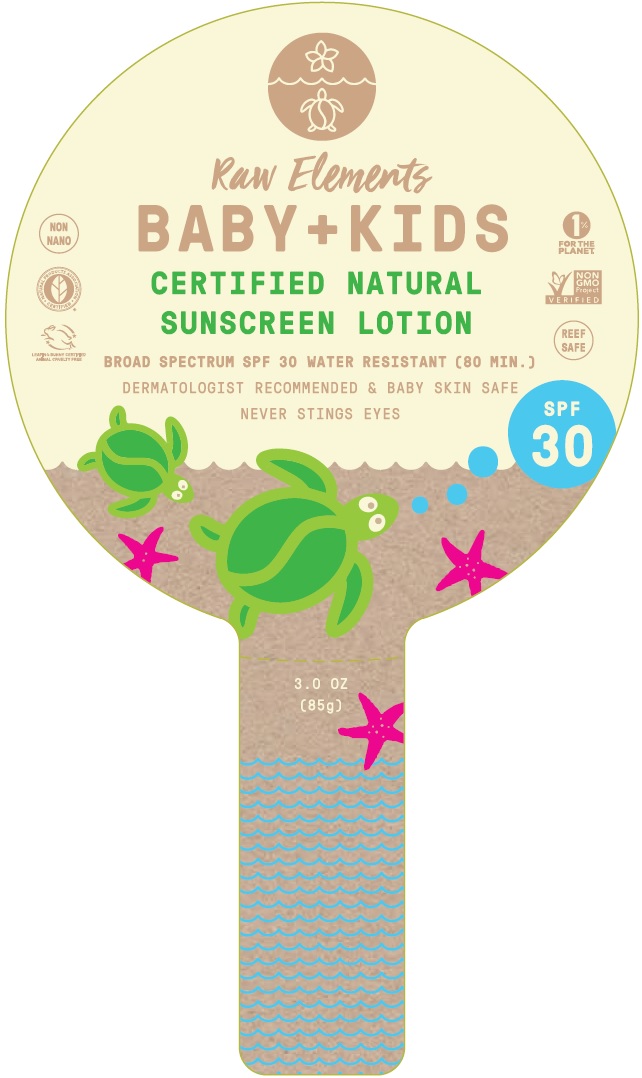 DRUG LABEL: Raw Elements Baby Kids Broad Spectrum SPF30
NDC: 70680-307 | Form: LOTION
Manufacturer: Raw Elements LLC
Category: otc | Type: HUMAN OTC DRUG LABEL
Date: 20231109

ACTIVE INGREDIENTS: ZINC OXIDE 250 mg/1 g
INACTIVE INGREDIENTS: SUNFLOWER OIL; YELLOW WAX; CALENDULA OFFICINALIS FLOWER; ROSEMARY; TOCOPHEROL

Raw Elements Baby+Kids Broad Spectrum SPF30 Lotion

Active Ingredients

Non-Nano Zinc Oxide 25%

Purpose

Sunscreen

Uses

- helps prevent sunburn
- If used as directed with other sun protection measures (see Directions), decreases the risk of skin cancer and early skin aging caused by the sun

Warnings

For external use only.

Do not use

on damaged or broken skin.

When using this product

keep out of eyes. Rinse with water to remove.

Stop use and ask a doctor

if rash occurs.

Keep out of reach of children.

If product is swallowed, get medical help or contact a Poison Control Center right away.

Directions

- apply liberally 15 minutes before sun exposure, reapply: after 80 minutes of swimming or sweating, immediately after towel drying, at least every 2 hours

- Sun Protection Measures. Spending time in the sun increases your risk of skin cancer and early skin aging. To decrease this risk, regularly use a sunscreen with a broad spectrum SPF of 15 or higher and other sun protection measures including:
- limit time in the sun, especially from 10 am-2 pm
- wear long-sleeve shirts, pants, hats, and sunglasses
- children under 6 months: Ask a doctor

Inactive ingredients

Helianthus Annuus (Organic Sunflower) Seed Oil, Cera Alba (Organic Beeswax), Cocos Nucifera (Organic Coconut) Oil, Theobroma Cacao (Organic Cocoa) Seed Butter, Calendula Officinalis (Organic Calendula) Flower Extract, Organic Chamomilla Recutita (Organic Chamomile) Flower Extract, Rosmarinus Officinalis (Natural Rosemary) Leaf Extract, Tocopherol (Natural Sunflower Vitamin E)

Other information

- protect this product from excessive heat and direct sun

Questions or comments?

Call toll free 1-888-442-6676